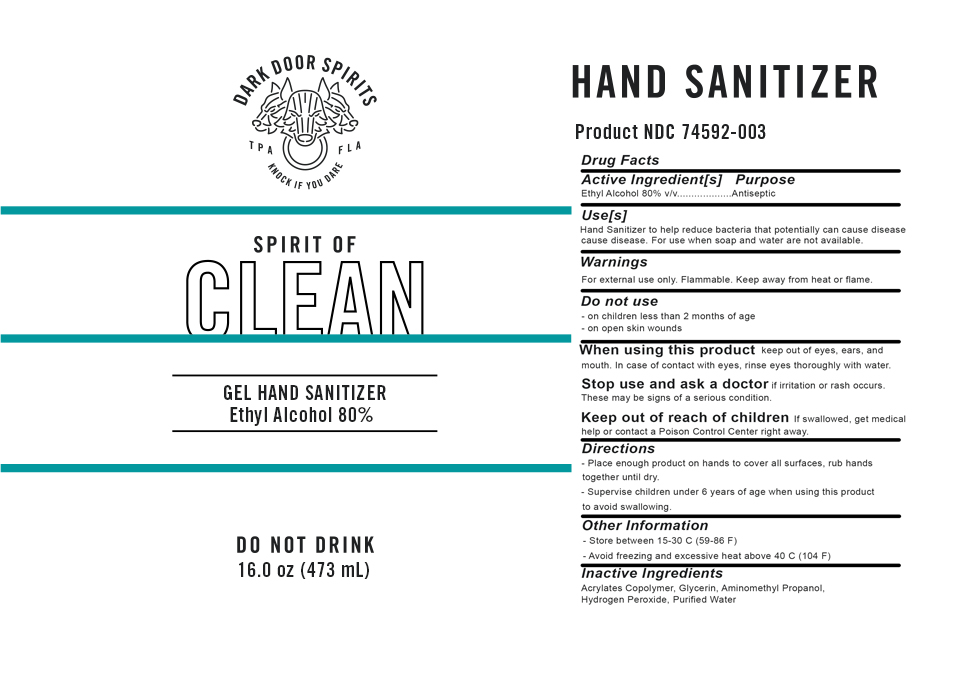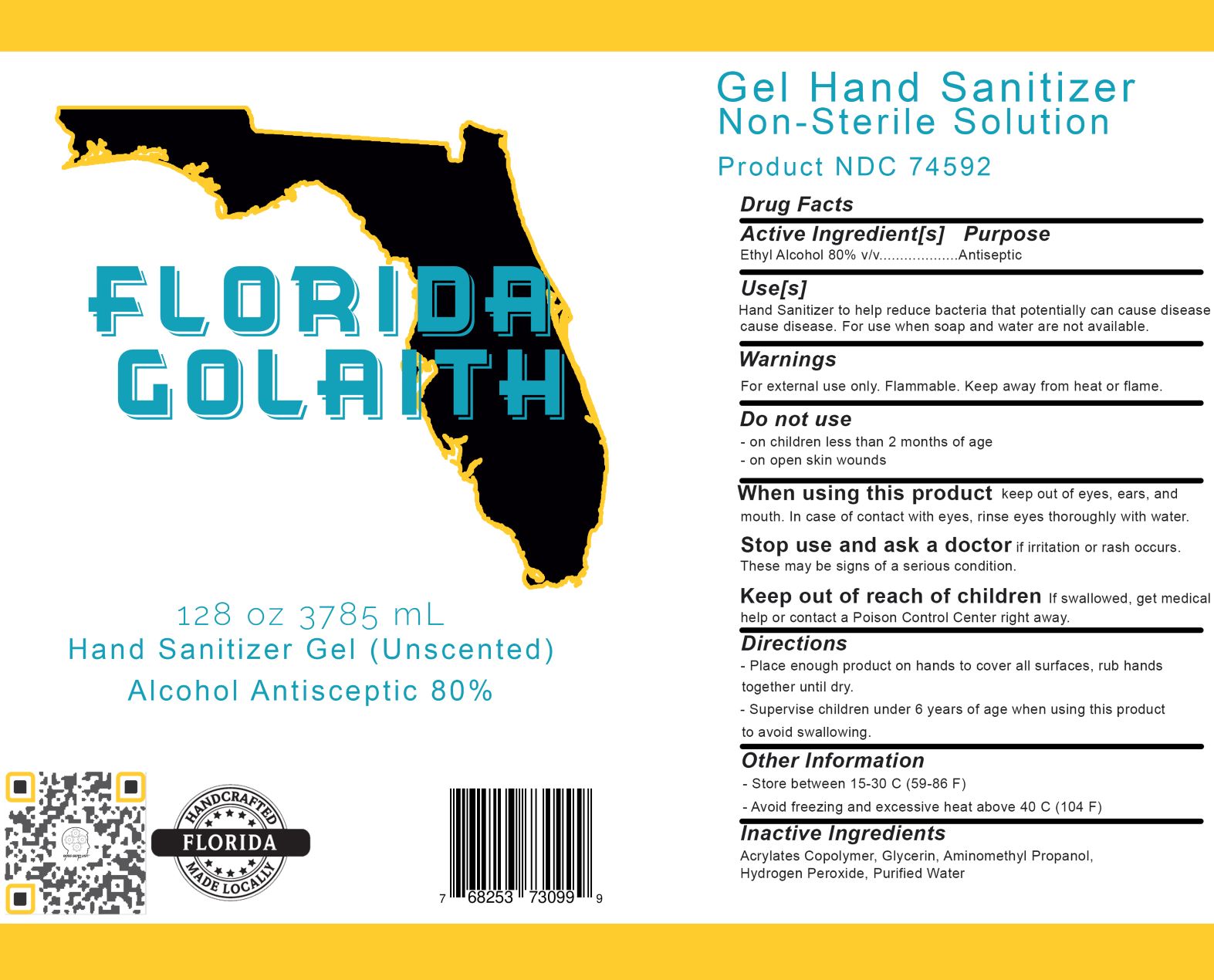 DRUG LABEL: Hand Sanitizer Gel
NDC: 74592-003 | Form: GEL
Manufacturer: Cerberus Craft Distillery LLC
Category: otc | Type: HUMAN OTC DRUG LABEL
Date: 20201121

ACTIVE INGREDIENTS: ALCOHOL 80 mL/1 g
INACTIVE INGREDIENTS: AMINOMETHYL PROPANEDIOL 0.6 mL/1 g; GLYCERIN 1.45 mL/1 g; HYDROGEN PEROXIDE 0.125 mL/1 g; SODIUM ACRYLATE/SODIUM ACRYLOYLDIMETHYLTAURATE COPOLYMER (4000000 MW) 5 mL/1 g

Hand Sanitizer gel 80%